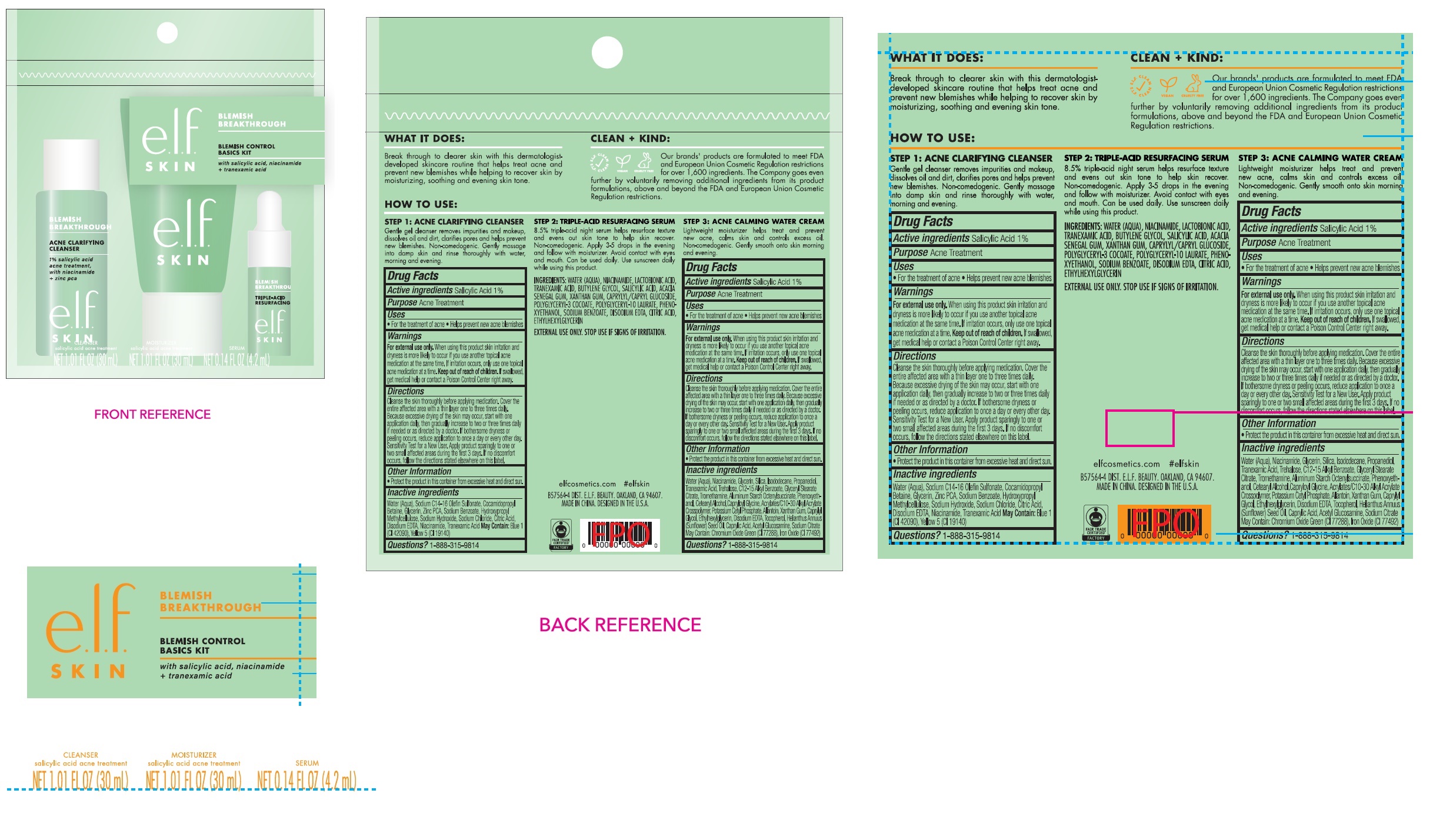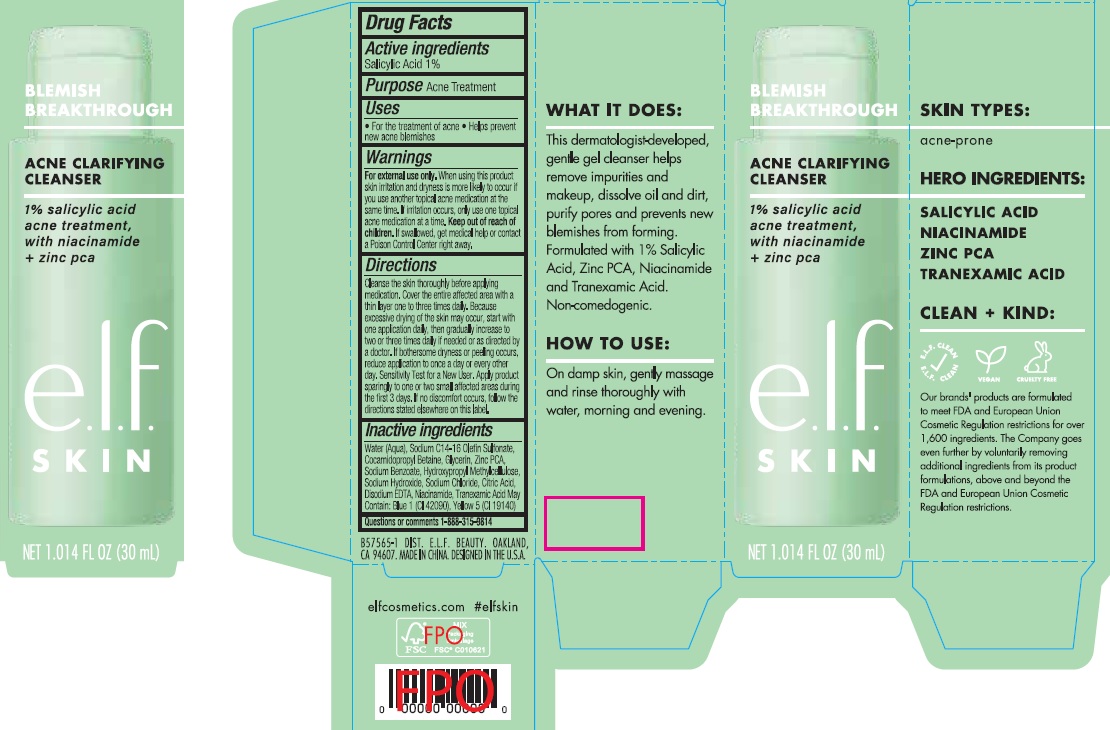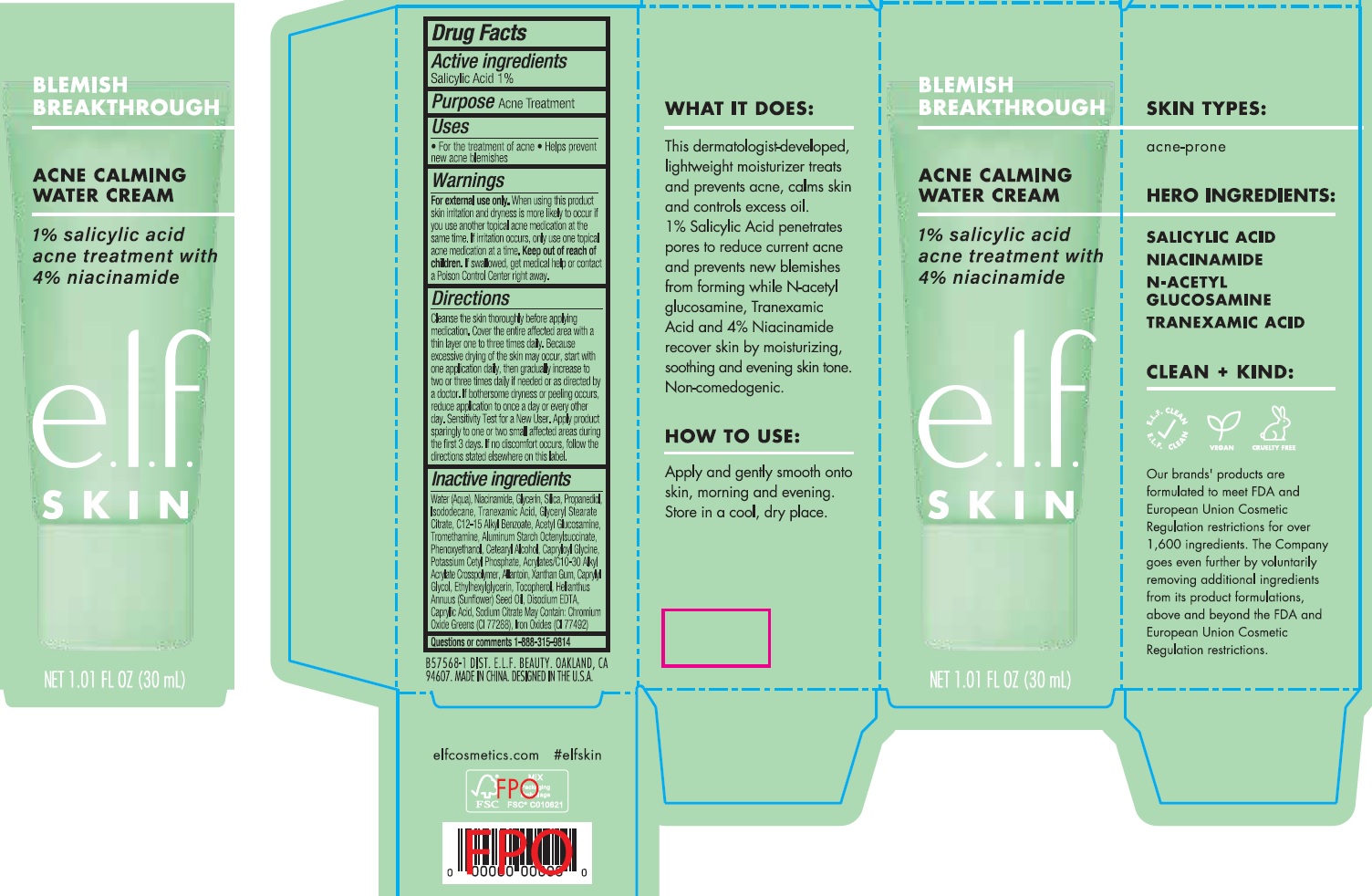 DRUG LABEL: Blemish Control Basics Kit
NDC: 76354-417 | Form: KIT | Route: TOPICAL
Manufacturer: e.l.f. Cosmetics, Inc
Category: otc | Type: HUMAN OTC DRUG LABEL
Date: 20251021

ACTIVE INGREDIENTS: SALICYLIC ACID 10 mg/1 mL; SALICYLIC ACID 10 mg/1 mL
INACTIVE INGREDIENTS: COCAMIDOPROPYL BETAINE; GLYCERIN; ZINC PIDOLATE; SODIUM BENZOATE; HYPROMELLOSE, UNSPECIFIED; SODIUM HYDROXIDE; SODIUM CHLORIDE; CITRIC ACID MONOHYDRATE; EDETATE DISODIUM ANHYDROUS; NIACINAMIDE; TRANEXAMIC ACID; WATER; SODIUM C14-16 OLEFIN SULFONATE; WATER; NIACINAMIDE; GLYCERIN; SILICON DIOXIDE; PROPANEDIOL; ISODODECANE; TRANEXAMIC ACID; GLYCERYL STEARATE CITRATE; ALKYL (C12-15) BENZOATE; N-ACETYLGLUCOSAMINE; TROMETHAMINE; ALUMINUM STARCH OCTENYLSUCCINATE; PHENOXYETHANOL; CETOSTEARYL ALCOHOL; CAPRYLOYL GLYCINE; POTASSIUM CETYL PHOSPHATE; ALLANTOIN; XANTHAN GUM; CAPRYLYL GLYCOL; ETHYLHEXYLGLYCERIN; TOCOPHEROL; SUNFLOWER OIL; EDETATE DISODIUM ANHYDROUS; CAPRYLIC ACID; SODIUM CITRATE

Blemish Control Basics Kit

Active ingredients

Salicylic Acid 1%

Purpose

Acne Treatment

Uses

- For the treatment of acne
- Helps prevent new acne blemishes

Warnings

For external use only.

When using this product

skin irritation and dryness is more likely to occur if you use another topical acne medication at the same time. If irritation occurs, only use one topical acne medication at a time.

Keep out of reach of children.

If swallowed, get medical help or contact a Poison Control Center right away.

Directions

Cleanse the skin thoroughly before applying medication. Cover the entire affected area with a thin layer one to three times daily. Because excessive drying of the skin may occur, start with one application daily, then gradually increase to two or three times daily if needed or as directed by a doctor. If bothersome dryness or peeling occurs, reduce application to once a day or every other day. Sensitivity Test for a New User. Apply product sparingly to one or two small affected areas during the first 3 days. If no discomfort occurs, follow the directions stated eleswhere on this label.

Inactive ingredients

Water (Aqua), Sodium C14-16 Olefin Sulfonate, Cocamidopropyl Betaine, Glycerin, Zinc PCA, Sodium Benzoate, Hydroxypropyl Methylcellulose, Sodium Hydroxide, Sodium Chloride, Citric Acid, Disodium EDTA, Niacinamide, Tranexamic Acid May Contain: Blue 1 (CI 42090), Yellow 5 (CI 19140)

Questions or comments

1-888-315-9814

Active ingredients

Salicylic Acid 1%

Purpose

Acne Treatment

Uses

- For the treatment of acne
- Helps prevent new acne blemishes

Warnings

For external use only.

When using this product

skin irritation and dryness is more likely to occur if you use another topical acne medication at the same time. If irritation occurs, only use one topical acne medication at a time.

Keep out of reach of children.

If swallowed, get medical help or contact a Poison Control Center right away.

Directions

Cleanse the skin thoroughly before applying medication. Cover the entire affected area with a thin layer one to three times daily. Because excessive drying of the skin may occur, start with one application daily, then gradually increase to two or three times daily if needed or as directed by a doctor. If bothersome dryness or peeling occurs, reduce application to once a day or every other day. Sensitivity Test for a New User. Apply product sparingly to one or two small affected areas during the first 3 days. If no discomfort occurs, follow the directions stated eleswhere on this label.

Inactive ingredients

Water (Aqua), Niacinamide, Glycerin, Silica, Propanediol, Isododecane, Tranexamic Acid, Glyceryl Stearate Citrate, C12-15 Alkyl Benzoate, Acetyl Glucosamine, Tromethamine, Aluminum Starch Octenylsuccinate, Phenoxyethanol, Cetearyl Alcohol, Capryloyl Glycine, Potassium Cetyl Phosphate, Acrylates/C10-30 Alkyl Acrylate Crosspolymer, Allantoin, Xanthan Gum, Caprylyl Glycol, Ethylhexylglycerin, Tocopherol, Helianthus Annuus (Sunflowe) Seed Oil, Disodium EDTA, Caprylic Acid, Sodium Citrate May Contain: Chromium Oxide Greens (CI 77288), Iron Oxides (CI 77492)

Questions or comments

1-888-315-9814